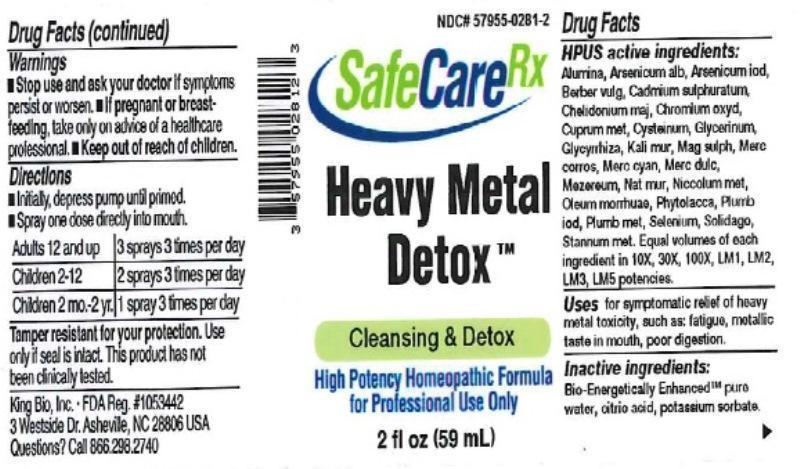 DRUG LABEL: Heavy Metal Detox
NDC: 57955-0281 | Form: LIQUID
Manufacturer: King Bio Inc.
Category: homeopathic | Type: HUMAN OTC DRUG LABEL
Date: 20150829

ACTIVE INGREDIENTS: ALUMINUM OXIDE 10 [hp_X]/59 mL; ARSENIC TRIOXIDE 10 [hp_X]/59 mL; ARSENIC TRIIODIDE 10 [hp_X]/59 mL; BERBERIS VULGARIS ROOT BARK 10 [hp_X]/59 mL; CADMIUM SULFIDE 10 [hp_X]/59 mL; CHELIDONIUM MAJUS 10 [hp_X]/59 mL; CHROMIC OXIDE 10 [hp_X]/59 mL; COPPER 10 [hp_X]/59 mL; CYSTEINE 10 [hp_X]/59 mL; GLYCERIN 10 [hp_X]/59 mL; GLYCYRRHIZA GLABRA 10 [hp_X]/59 mL; POTASSIUM CHLORIDE 10 [hp_X]/59 mL; MAGNESIUM SULFATE HEPTAHYDRATE 10 [hp_X]/59 mL; MERCURIC CHLORIDE 10 [hp_X]/59 mL; MERCURIC CYANIDE 10 [hp_X]/59 mL; CALOMEL 10 [hp_X]/59 mL; DAPHNE MEZEREUM BARK 10 [hp_X]/59 mL; SODIUM CHLORIDE 10 [hp_X]/59 mL; NICKEL 10 [hp_X]/59 mL; COD LIVER OIL 10 [hp_X]/59 mL; PHYTOLACCA AMERICANA ROOT 10 [hp_X]/59 mL; LEAD IODIDE 10 [hp_X]/59 mL; LEAD 10 [hp_X]/59 mL; SELENIUM 10 [hp_X]/59 mL; SOLIDAGO VIRGAUREA FLOWERING TOP 10 [hp_X]/59 mL; TIN 10 [hp_X]/59 mL
INACTIVE INGREDIENTS: WATER; POTASSIUM SORBATE; ANHYDROUS CITRIC ACID

Heavy Metal Detox™

ACTIVE INGREDIENT

Drug Facts__________________________________________________________________________________________________________

HPUS active ingredients: Alumina, Arsenicum album, Arsenicum iodatum, Berberis vulgaris, Cadmium sulphuratum, Chelidonium majus, Chromium oxydatum, Cuprum metallicum, Cysteinum, Glycerinum, Glycyrrhiza glabra, Kali muriaticum, Magnesia sulphurica, Mercurius corrosivus, Mercurius cyanatus, Mercurius dulcis, Mezereum, Natrum muriaticum, Niccolum metallicum, Oleum morrhuae, Phytolacca decandra, Plumbum iodatum, Plumbum metallicum, Selenium metallicum, Solidago virgaurea, Stannum metallicum. Equal volumes of each ingredient in 10X, 30X, 100X, LM1, LM2, LM3, LM5 potencies.

INDICATIONS AND USAGE

Uses for symptomatic relief of heavy metal toxicity, such as: fatigue, metallic taste in mouth, poor digestion.

Inactive Ingredients:

Bio-Energetically Enhanced™ pure water, citric acid and potassium sorbate.

Warnings

- Stop use and ask your doctor if symptoms persist or worsen.
- If pregnant or breast-feeding, take only on advice of a healthcare professional.

- Keep out of reach of children.

Directions

- Initially, depress pump until primed.
- Spray one dose directly into mouth.
- Adults 12 and up: 3 sprays 3 times per day.
- Children 2-12: 2 sprays 3 times per day.
- Children 2 mo-2yr: 1 spray 3 times per day.

OTHER SAFETY INFORMATION

Tamper resistant for your protection. Use only if safety seal is intact. This product has not been clinically tested.

PURPOSE

Uses for symptomatic relief of heavy metal toxicity, such as:

- fatigue
- metallic taste in mouth
- poor digestion